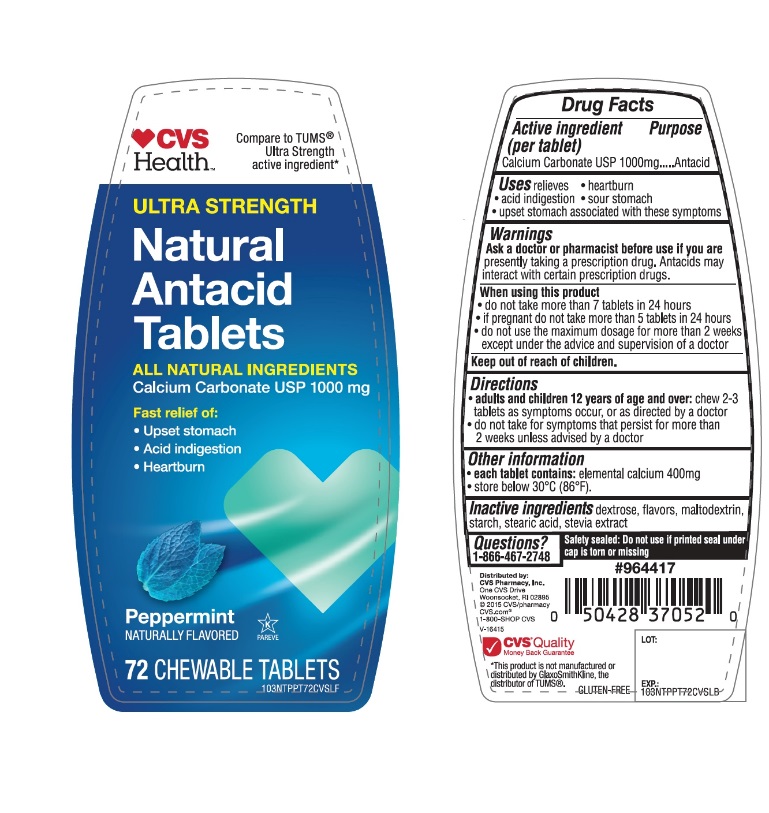 DRUG LABEL: CVS Health Ultra Strength Natural Antacid

NDC: 59779-675 | Form: TABLET, CHEWABLE
Manufacturer: CVS Pharmacy,Inc.
Category: otc | Type: HUMAN OTC DRUG LABEL
Date: 20251204

ACTIVE INGREDIENTS: CALCIUM CARBONATE 1000 mg/1 1
INACTIVE INGREDIENTS: DEXTROSE, UNSPECIFIED FORM; MALTODEXTRIN; STARCH, CORN; STEARIC ACID; STEVIA REBAUDIANA LEAF

CVS Health Ultra Strength Natural Antacid Tablets

Active ingredient (per tablet)

Calcium Carbonate USP 1000mg

Purpose

Antacid

Uses

relieves

- heartburn
- acid indigestion
- sour stomach
- upset stomach associated with these symptoms

Warnings

Ask a doctor or pharmacist before use if you arepresently taking a prescription drug. Antacids may interact with certain prescription drugs.

When using this product

- do not take more than 7 tablets in 24 hours
- if pregnant do not take more than 5 tablets in 24 hours
- do not use the maximum dosage for more than 2 weeks except under the advice and supervision of a doctor.

Directions

- adults and children 12 years of age and over:chew 2-3 tablets as symptoms occur, or as directed by a doctor
- do not take for symptoms that persist for more than 2 weeks unless advised by a doctor

Other information

- each tablet contains:elemental calcium 400mg
- store below 30°C (86°F).

Inactive ingredients

dextrose unspecified form, flavors, maltodextrin, starch, stearic acid, stevia extract

Questions?

1-866-467-2748

Safety sealed: Do not use if printed seal under cap is torn or missing

Package/Label Principal Display Panel

CVS Health™

Compare to TUMS®Ultra Strength active ingredient*

Ultra Strength

Natural

Antacid

Tablets

ALL NATURAL INGREDIENTS

Calcium Carbonate USP 1000 mg

Fast relief of:

- Upset stomach
- Acid indigestion
- Heartburn

Peppermint

NATURALLY FLAVORED

72 CHEWABLE TABLETS

GLUTEN- FREE

Distributed by:

CVS Pharmacy,Inc.

One CVS Drive

Woonsocket,RI 02895

©2015 CVS/pharmacy

CVS.com®

1-800-SHOP CVS

V-16415

CVS Quality

Money Back Guarantee

*This product is not manufactured or distributed by GlaxoSmithKline, the distributor of TUMS®.

GLUTEN- FREE